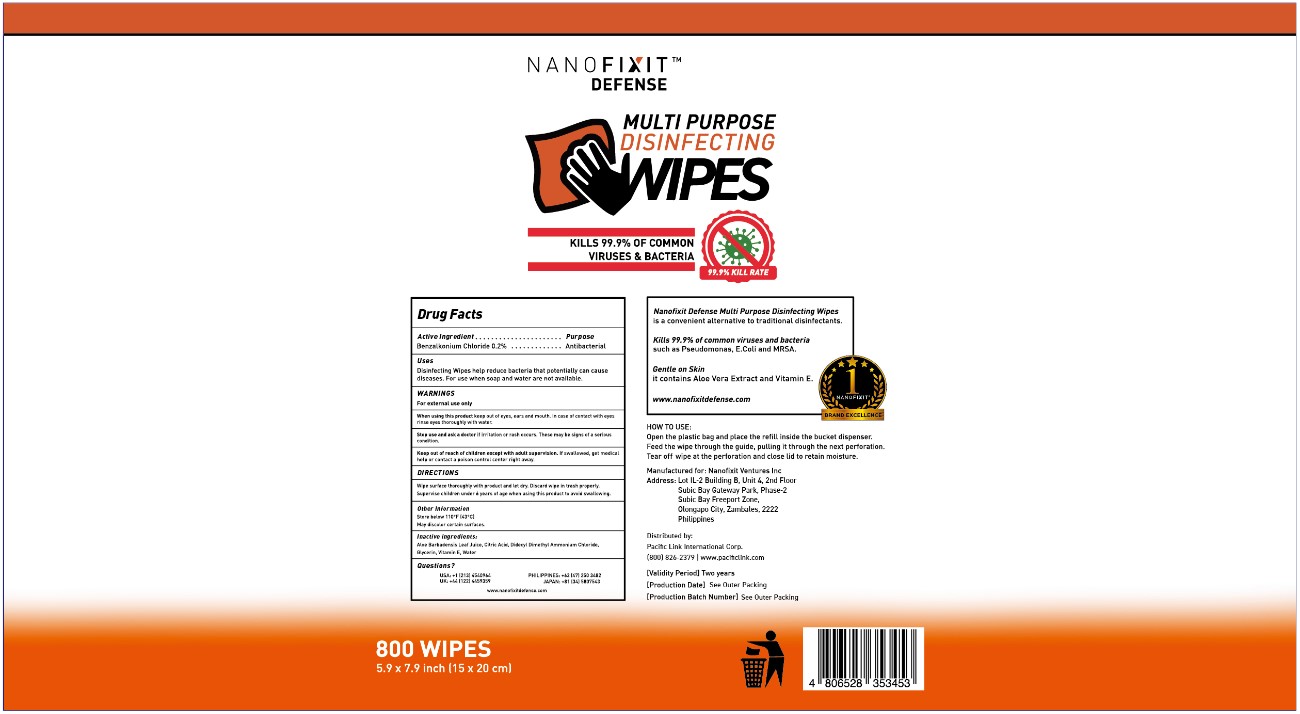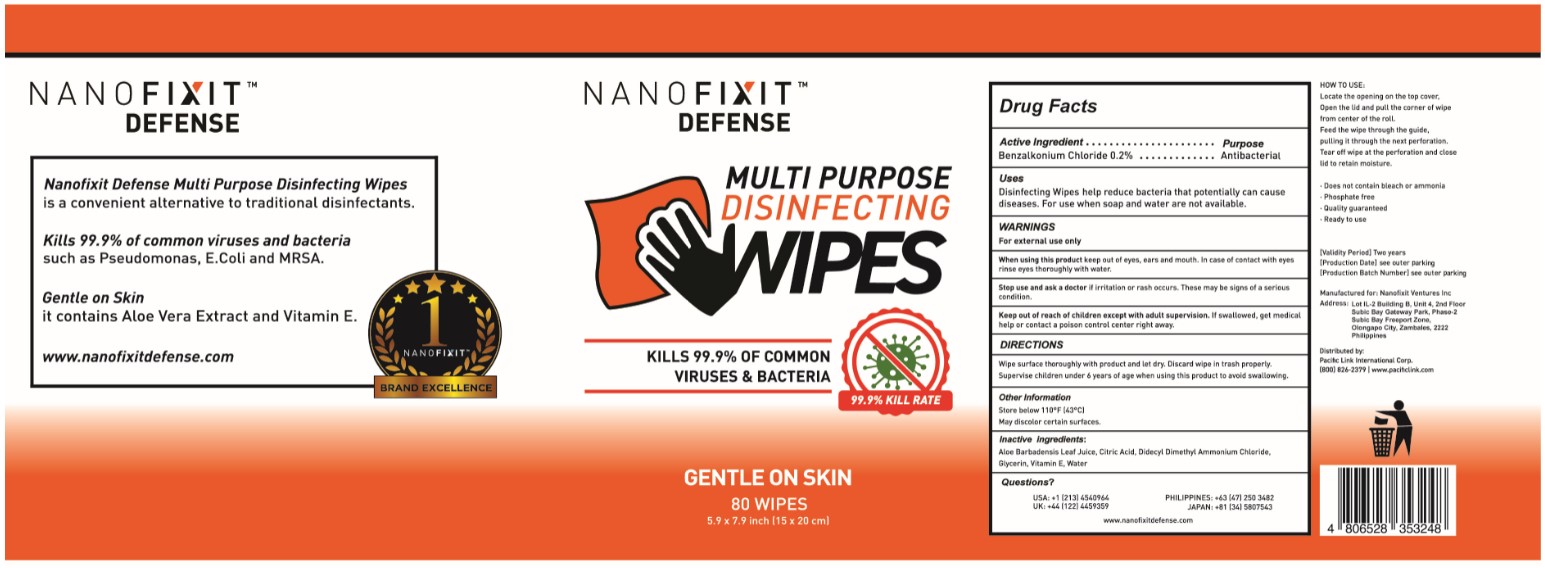 DRUG LABEL: Disinfecting wipes
NDC: 92763-004 | Form: CLOTH
Manufacturer: Nanofixit Ventures Inc.
Category: otc | Type: HUMAN OTC DRUG LABEL
Date: 20200730

ACTIVE INGREDIENTS: BENZALKONIUM CHLORIDE 0.2 g/100 g
INACTIVE INGREDIENTS: TOCOPHEROL 0.0025 g/100 g; DIDECYLDIMONIUM CHLORIDE 0.16 g/100 g; ANHYDROUS CITRIC ACID 0.01 g/100 g; GLYCERIN 0.1 g/100 g; ALOE 0.0025 g/100 g; WATER 99.525 g/100 g

Active Ingredient(s)

Benzalkonium chloride 0.2% w/w. Purpose: Antiseptic

Purpose

Antiseptic, Hand Sanitizer

Use

Disinfecting Wipes help reduce bacteria that potentially can cause disease. For use when soap and water are not available.

Warnings

For external use only.

Do not use

- in children less than 2 months of age
- on open skin wounds

When using this product keep out of eyes, ears, and mouth. In case of contact with eyes, rinse eyes thoroughly with water.
Stop use and ask a doctor if irritation or rash occurs. These may be signs of a serious condition.
Keep out of reach of children. If swallowed, get medical help or contact a Poison Control Center right away.

Stop use and ask a doctor if irritation or rash occurs. These may be signs of a serious condition.

Keep out of reach of children except with adult supervision. If swallowed, get medical help or contact a Poison Control Center right away.

Directions

- Wipe surface thoroughly with product and let dry. Discard wipe in trash properly.
- Supervise children under 6 years of age when using this product to avoid swallowing.

Inactive ingredients

Aloe Barbadensis Leaf Juice, Citric Acid, Didecyl Dimethyl Ammonium Chloride, Glycerin, Vitamin E, Water.

Package Label - Principal Display Panel

80 WIPES in 1 PIAL NDC: 92763-004-01

Package Label - Principal Display Panel

800 WIPES in 1 BAG NDC: 92763-004-02